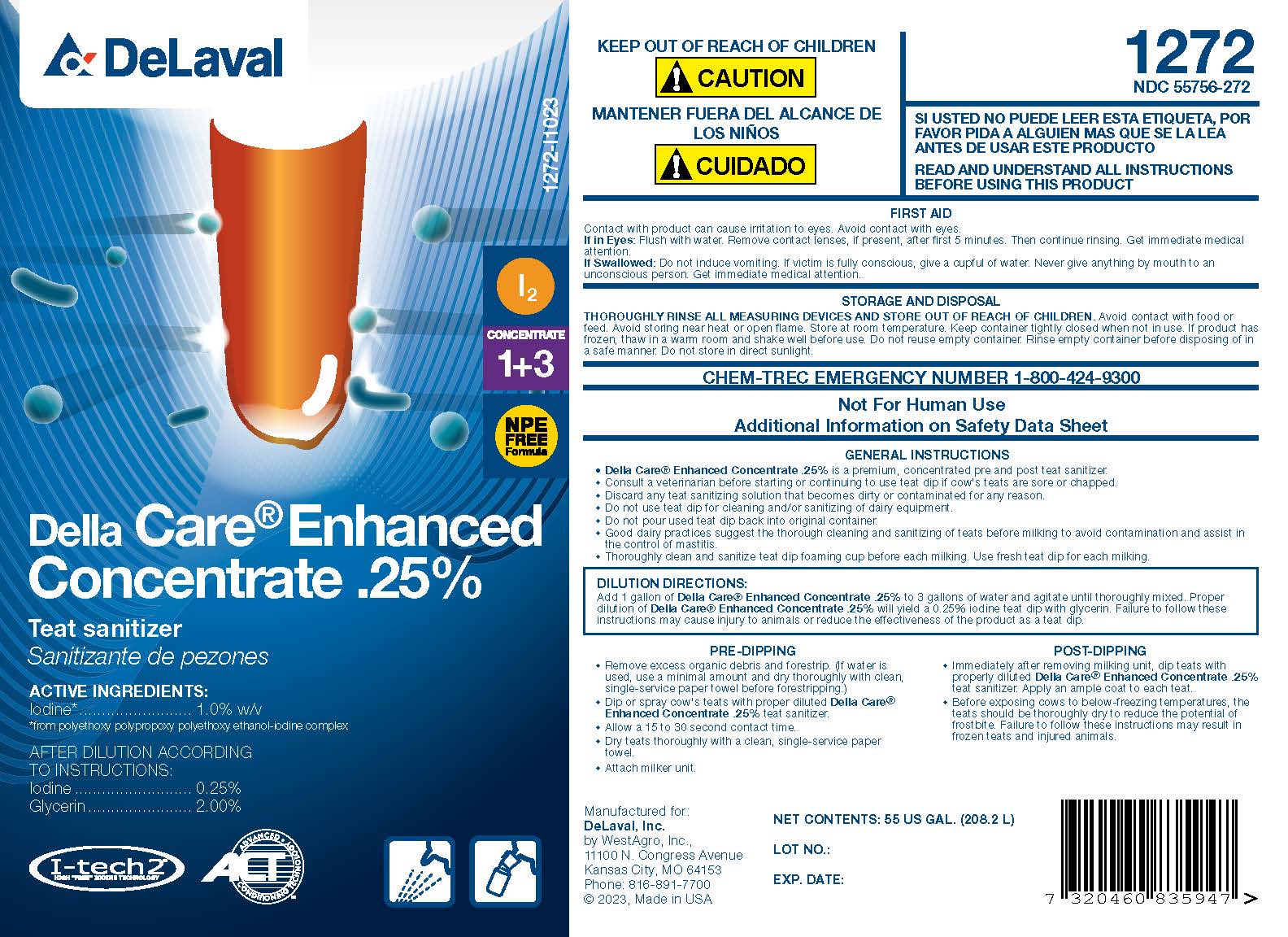 DRUG LABEL: Della Care Enhanced Concentrate .25%
NDC: 55756-272 | Form: SOLUTION, CONCENTRATE
Manufacturer: Delaval
Category: animal | Type: OTC ANIMAL DRUG LABEL
Date: 20231019

ACTIVE INGREDIENTS: IODINE 10.4 g/1 L

Della Care® Enhanced Concentrate .25%

Teat Sanitizer

Sanitizante de pezones

ACTIVE INGREDIENTS:
Iodine* .......................... 1.0%w/v
*from polyethoxy polypropoxy polyethoxy ethanol-iodine complex

AFTER DILUTION ACCORDING TO INSTRUCTIONS:
Iodine ........................ 0.25%
Glycerin ..................... 2.00%

I-tech 2
HIGH "FREE" IODINE TECHNOLOGY

ACT ADVANCED CONDITIONING TECHNOLOGY

KEEP OUT OF REACH OF CHILDREN

! CAUTION

MANTENER FUERA DEL ALCANCE DE LOS NINOS

! CUIDADO

SI USTED NO PUEDE LEER ESTA ETIQUETA, POR FAVOR PIDA A ALGUIEN MAS QUE SE LA LEA ANTES DE USAR ESTE PRODUCTO

READ AND UNDERSTAND ALL INSTRUCTIONS BEFORE USING THIS PRODUCT

FIRST AID

Contact with product can cause irritation to eyes. Avoid contact with eyes.
If in Eyes: Flush with water. Remove contact lenses, if present, after the first 5 minutes. Then continue rinsing. Get immediate medical attention.
If Swallowed: Do not induce vomiting. If victim is fully conscious, give a cupful of water. Never give anything by mouth to an unconscious person. Get immediate medical attention.

STORAGE AND DISPOSAL

THOROUGHLY RINSE ALL MEASURING DEVICES AND STORE OUT OF REACH OF CHILDREN. Avoid contact with food or feed. Avoid storing near heat or open flame. Store at room temperature. Keep container tightly closed when not in use. If product has frozen, thaw in a warm room and shake well before use. Do not reuse empty container. Rinse empty container before disposing of in a safe manner. Do not store in direct sunlight.

CHEM-TREC EMERGENCY NUMBER 1-800-424-9300

Not For Human Use

Additional Information on Material Safety Data Sheet

INDICATIONS AND USAGE

GENERAL INSTRUCTIONS

- Della Care® Enhanced Concentrate .25% is a premium, concentrated pre and post teat sanitizer.
- Consult a veterinarian before starting or continuing to use teat dip if cow's teats are sore or chapped.
- Discard any teat sanitizing solution that becomes dirty or contaminated for any reason.
- Do not use teat dip for cleaning and/or sanitizing of dairy equipment.
- Do not pour used teat dip back into original container.
- Good dairy practices suggest the thorough cleaning and sanitizing of teats before milking to avoid contamination and assist in the control of mastitis.
- Thoroughly clean and sanitize teat dip foaming cup before each milking. Use fresh teat dip for each milking.

DILUTION DIRECTIONS:

Add 1 gallon of Della Care® Enhanced Concentrate .25% to 3 gallons of water and agitate until thoroughly mixed. Proper dilution of Della Care® Enhanced Concentrate .25% will yield a 0.25% iodine teat dip with glycerin. Failure to follow these instructions may cause injury to animals or reduce the effectiveness of the product as a teat dip.

PRE-DIPPING

- Remove excess organic debris and forestrip. (If water is used, use a minimal amount and dry thoroughly with clean, single-service paper towel before forestripping.)
- Dip or spray cow's teats with proper diluted Della Care® Enhanced Concentrate .25% teat sanitizer.
- Allow a 15 to 30 second contact time.
- Dry teat thoroughly with a clean, single-service paper towel.
- Attach milker unit.

POST-DIPPING

- Immediately after removing milking unit, dip teats with properly diluted Della Care Enhanced Concentrate .25% teat sanitizer. Apply an ample coat to each teat.
- Before exposing cows to below-freezing temperatures, the teats should be thoroughly dry to reduce the potential of frostbite. Failure to follow these instructions may result in frozen teats and injured animals.

Manufactured for:
DeLaval, Inc.

by WestAgro, Inc.

11100 Congress Avenue

Kansas City, MO 64153

Phone: 816-891-7700

© 2023, Made in U.S.A.

NET CONTENTS:

LOT NO.:

EXP. DATE:

PACKAGE LABEL

Add image transcription here...